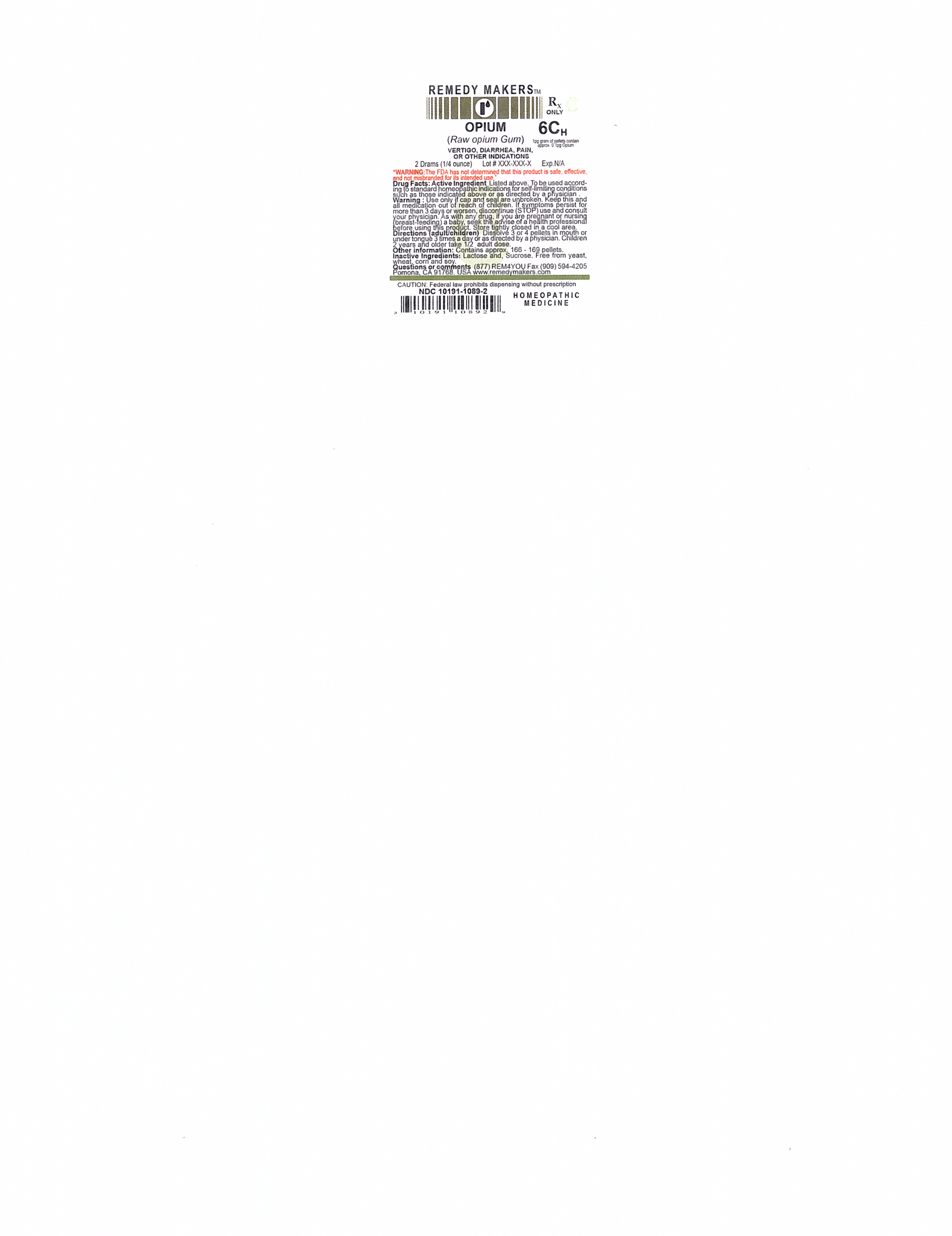 DRUG LABEL: OPIUM
NDC: 10191-1089 | Form: PELLET
Manufacturer: Remedy Makers
Category: homeopathic | Type: HUMAN PRESCRIPTION DRUG LABEL
Date: 20230307
DEA Schedule: CII

ACTIVE INGREDIENTS: OPIUM 6 [hp_C]/1 1
INACTIVE INGREDIENTS: SUCROSE; LACTOSE

CII

WARNING:

"The FDA has not determined that the product is safe, effective and not misbranded for its intended use."

INDICATION:

VERTIGO, DIARRHEA, PAIN, OR OTHER INDICATIONS

WARNING:

Use only if cap and seal are unbroken. Keep this and all medications out of reach of children. If symptoms persist for more than 3 days or worsen, discontinue (STOP) use and consult your physician. As with any drug. If you are pregnant or nursing (breast-feeding) a baby, seek the advise of a health professional before using this product. Store tightly closed in a cool area.

Directions (adult/children)

Disolve 3 or 4 pellets in mouth or under tongue 3 times a day or as directed by a physician. Children 2 years and older take 1/2 adult dose.

Other Information:

Contains approx. 166 - 169 pellets.

WARNINGS AND PRECAUTIONS

CAUTION: Federal law prohibits dispensing without prescription.